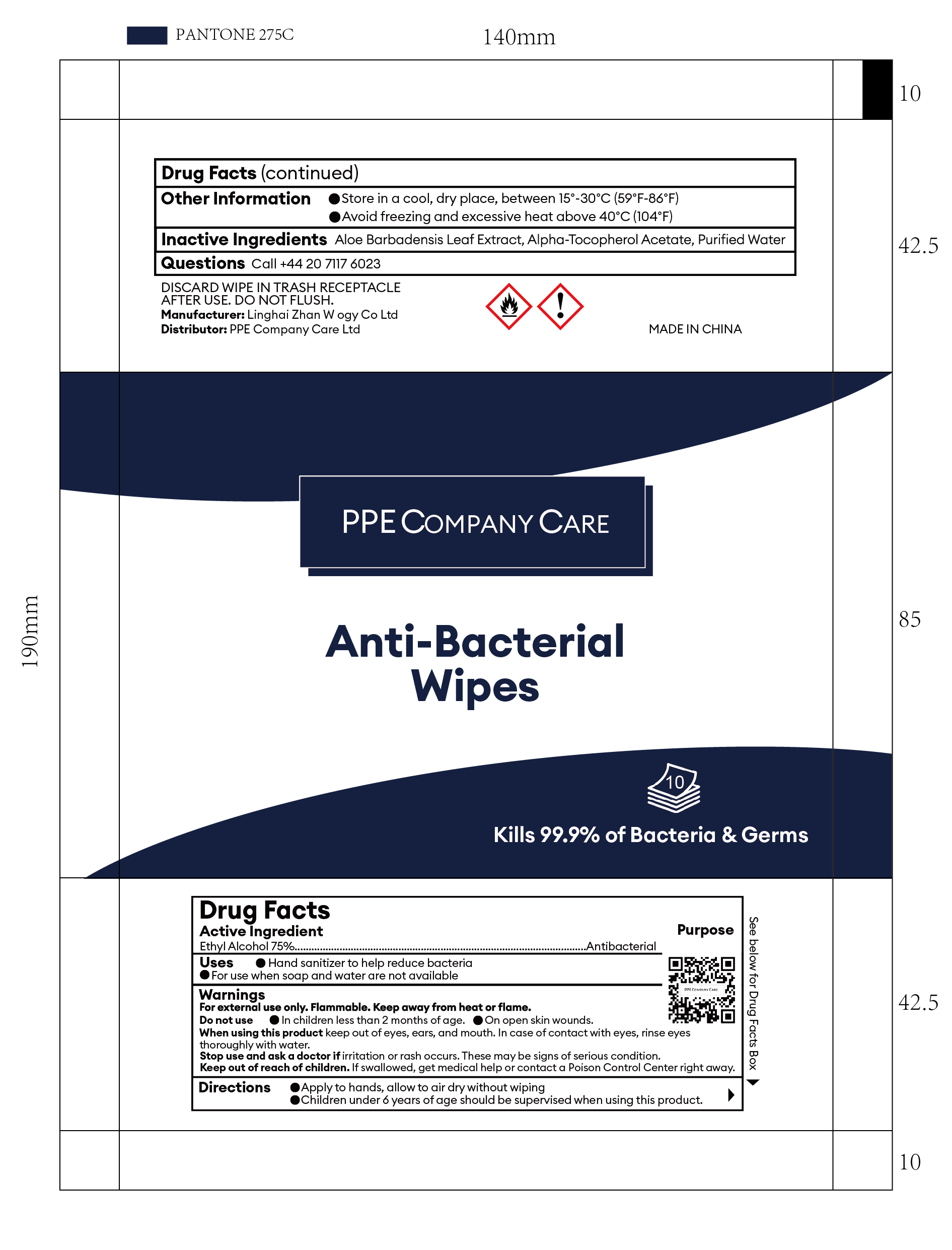 DRUG LABEL: PPE COMPANY CARE Anti-Bacterial Wipes
NDC: 80856-001 | Form: CLOTH
Manufacturer: PPE COMPANY CARE LTD
Category: otc | Type: HUMAN OTC DRUG LABEL
Date: 20231024

ACTIVE INGREDIENTS: ALCOHOL 75 mL/100 mL
INACTIVE INGREDIENTS: WATER; .ALPHA.-TOCOPHEROL ACETATE, D-; ALOE VERA LEAF

80856-001 PPE COMPANY CARE Anti-Bacterial Wipes

Active Ingredient

Ethyl Alcohol 75%

Purpose

Antibacterial

Uses

• Hand sanitizer to help reduce bacteria

• For use when soap and water are not available

Warnings

For external use only. Flammable. Keep away from heat or flame.

Do not use • In children less than 2 months of age. • On open skin wounds.

When using this product keep out of eyes, ears, and mouth. In case of contact with eyes, rinse eyes thoroughly with water.

Stop use and ask a doctor if irritation or rash occurs. These may be signs of serious condition.

Keep out of reach of children. If swallowed, get medical help or contact a Poison Control Center right away.

Do not use • In children less than 2 months of age. • On open skin wounds.

When using this product keep out of eyes, ears, and mouth. In case of contact with eyes, rinse eyes thoroughly with water.

Stop use and ask a doctor if irritation or rash occurs. These may be signs of serious condition.

Keep out of reach of children. If swallowed, get medical help or contact a Poison Control Center right away.

Directions

• Apply to hands, allow to air dry without wiping

• Children under 6 years of age should be supervised when using this product.

Other Information

• Store in a cool, dry place, between 15°-30°C (59°F-86°F)

• Avoid freezing and excessive heat above 40°C (104°F)

Inactive Ingredients

Aloe Barbadensis Leaf Extract, Alpha-Tocopherol Acetate, Purified Water

PACKAGE LABEL

10 Wipes, NDC: 80856-001-01